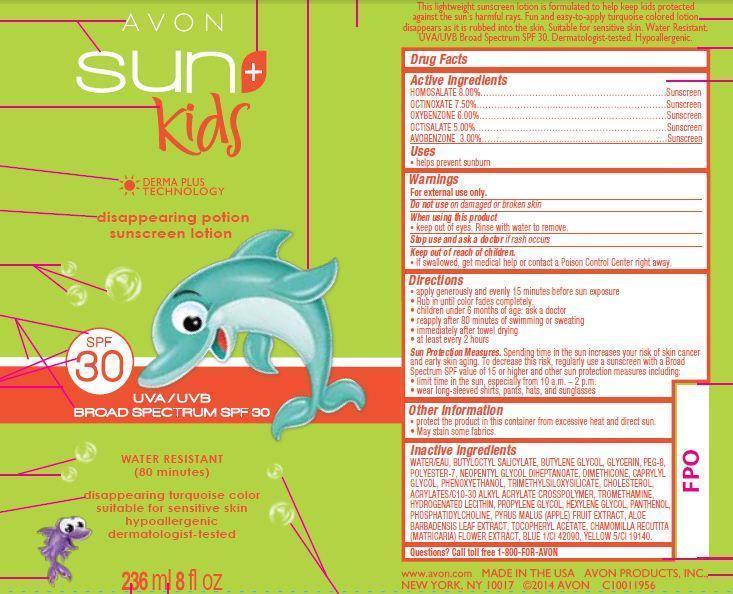 DRUG LABEL: Avon Sun Sport
NDC: 10096-0315 | Form: LOTION
Manufacturer: New Avon LLC
Category: otc | Type: HUMAN OTC DRUG LABEL
Date: 20160219

ACTIVE INGREDIENTS: HOMOSALATE 80 mg/1 mL; OCTINOXATE 75 mg/1 mL; OXYBENZONE 60 mg/1 mL; OCTISALATE 50 mg/1 mL; AVOBENZONE 30 mg/1 mL

Active ingredients

HOMOSALATE 8.00%……………………
OCTINOXATE 7.50%………………………
OXYBENZONE 6.00%……………………
OCTISALATE 5.00%………………………
AVOBENZONE 3.00%………………………

Purpose
.................................Sunscreen

.................................Sunscreen

.................................Sunscreen

.................................Sunscreen

.................................Sunscreen

Uses
• helps prevent sunburn

Warnings
For external use only

Do not use on damaged or broken skin

When using this product

- keep out of eyes. Rinse with water to remove.

Stop use and ask a doctor if rash occurs

Keep out of reach of children.

If swallowed, get medical help or contact a Poison Control Center right away.

Directions
• apply generously and evenly 15 minutes before sun exposure

• Rub in until color fades completely.
• children under 6 months of age: ask a doctor
• reapply after 80 minutes of swimming or sweating
• immediately after towel drying

• at least every 2 hours

• Sun Protection Measures. Spending time in the sun increases your risk of skin cancer and early skin aging. To decrease this risk, regularly use a sunscreen with a Broad Spectrum SPF value of 15 or higher and other sun protection measures including:
• limit time in the sun, especially from 10 a.m. – 2 p.m.
• wear long-sleeved shirts, pants, hats, and sunglasses

Other information

• protect the product in this container from excessive heat and direct sun

• May stain some fabrics.

Inactive Ingredients:
WATER/EAU, BUTYLOCTYL SALICYLATE, BUTYLENE GLYCOL, GLYCERIN, PEG-8, POLYESTER-7, NEOPENTYL GLYCOL DIHEPTANOATE, DIMETHICONE, CAPRYLYL GLYCOL, PHENOXYETHANOL, TRIMETHYLSILOXYSILICATE, CHOLESTEROL, ACRYLATES/C10-30 ALKYL ACRYLATE CROSSPOLYMER, TROMETHAMINE, HYDROGENATED LECITHIN, PROPYLENE GLYCOL, HEXYLENE GLYCOL, PANTHENOL, PHOSPHATIDYLCHOLINE, PYRUS MALUS (APPLE) FRUIT EXTRACT, ALOE BARBADENSIS LEAF EXTRACT, TOCOPHERYL ACETATE, CHAMOMILLA RECUTITA (MATRICARIA) FLOWER EXTRACT, BLUE 1/CI 42090, YELLOW 5/CI 19140 .

Questions?
Call toll free 1-800-FOR-AVON